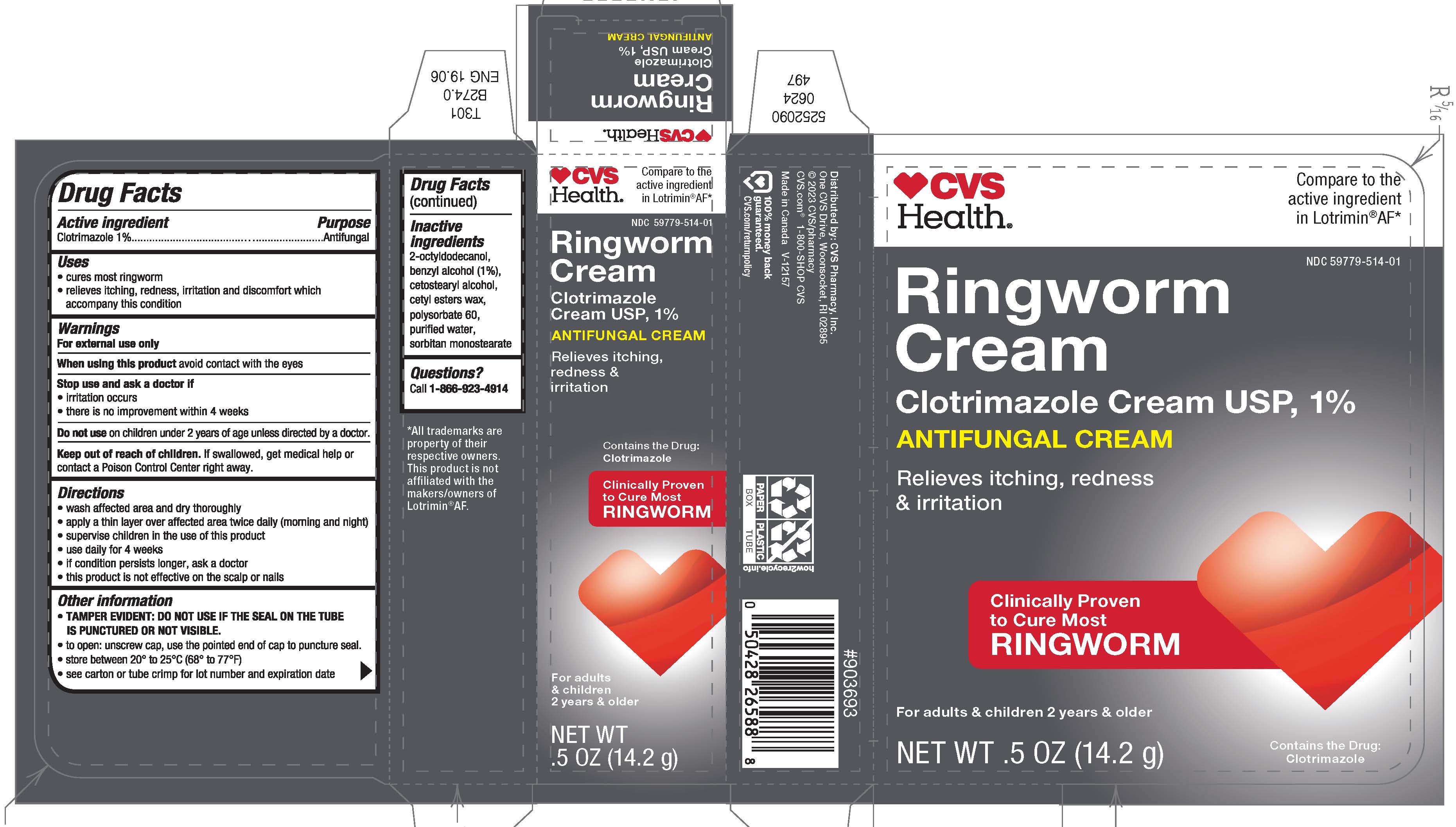 DRUG LABEL: CVS 


NDC: 59779-514 | Form: CREAM
Manufacturer: CVS Pharmacy
Category: otc | Type: HUMAN OTC DRUG LABEL
Date: 20250711

ACTIVE INGREDIENTS: CLOTRIMAZOLE 1 g/100 g
INACTIVE INGREDIENTS: BENZYL ALCOHOL; CETOSTEARYL ALCOHOL; CETYL ESTERS WAX; OCTYLDODECANOL; POLYSORBATE 60; WATER; SORBITAN MONOSTEARATE

CVS
Antifungal Ringworm

Drug Facts

Active ingredient

Clotrimazole 1%

Purpose

Antifungal

Uses

- cures most ringworm
- relieves itching, redness, irritation and discomfort which accompany this condition

Warnings

For external use only

When using this productavoid contact with the eyes

Stop use and ask a doctor if

- irritation occurs
- there is no improvement within 4 weeks

DO NOT USE

Do not useon children under 2 years of age unless directed by a doctor.

Keep out of reach of children.If swallowed, get medical help or contact a Poison Control Center right away.

Directions

- wash affected area and dry thoroughly
- apply a thin layer over affected area twice daily (morning and night)
- supervise children in the use of this product
- use daily for 4 weeks
- if condition persists longer, ask a doctor
- this product is not effective on the scalp or nails

Other information

- TAMPER EVIDENT: DO NOT USE IF THE SEAL ON THE TUBE IS PUNCTURED OR NOT VISIBLE.
- to open: unscrew cap, use the pointed end of cap to puncture seal.
- store between 20° to 25°C (68° to 77°F)
- see carton or tube crimp for lot number and expiration date

Inactive ingredients

benzyl alcohol (1%), cetostearyl alcohol, cetyl esters wax, 2-octyldodecanol, polysorbate 60, purified water, sorbitan monostearate

Questions?

Call 1-866-923-4914

Distributed by: CVS Pharmacy, Inc.
One CVS Drive, Woonsocket, RI 02895

PRINCIPAL DISPLAY PANEL - 14.2 g Tube Carton

CVS
Health®

Compare to the
active ingredient
in Lotrimin®AF*

NDC 59779-514-01

Ringworm
Cream
Clotrimazole Cream USP, 1%
ANTIFUNGAL CREAM

Relieves itching, redness
& irritation

Clinically Proven
to Cure Most
RINGWORM

For adults & children 2 years & older

Contains the Drug:
Clotrimazole

NET WT .5 OZ (14.2 g)